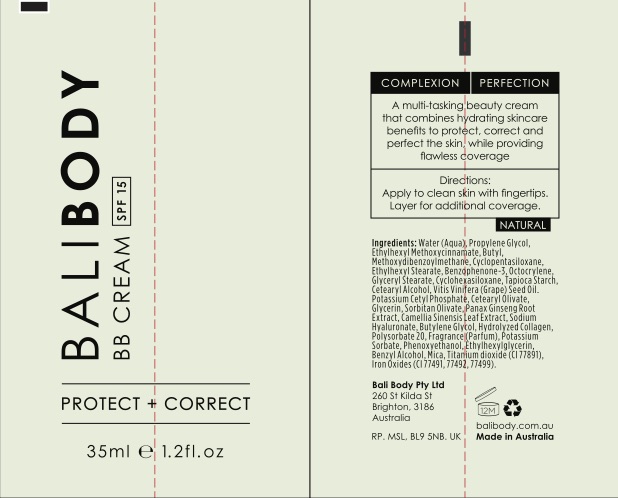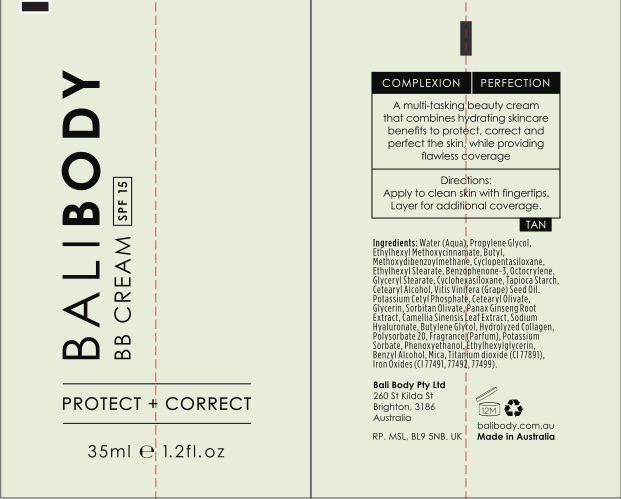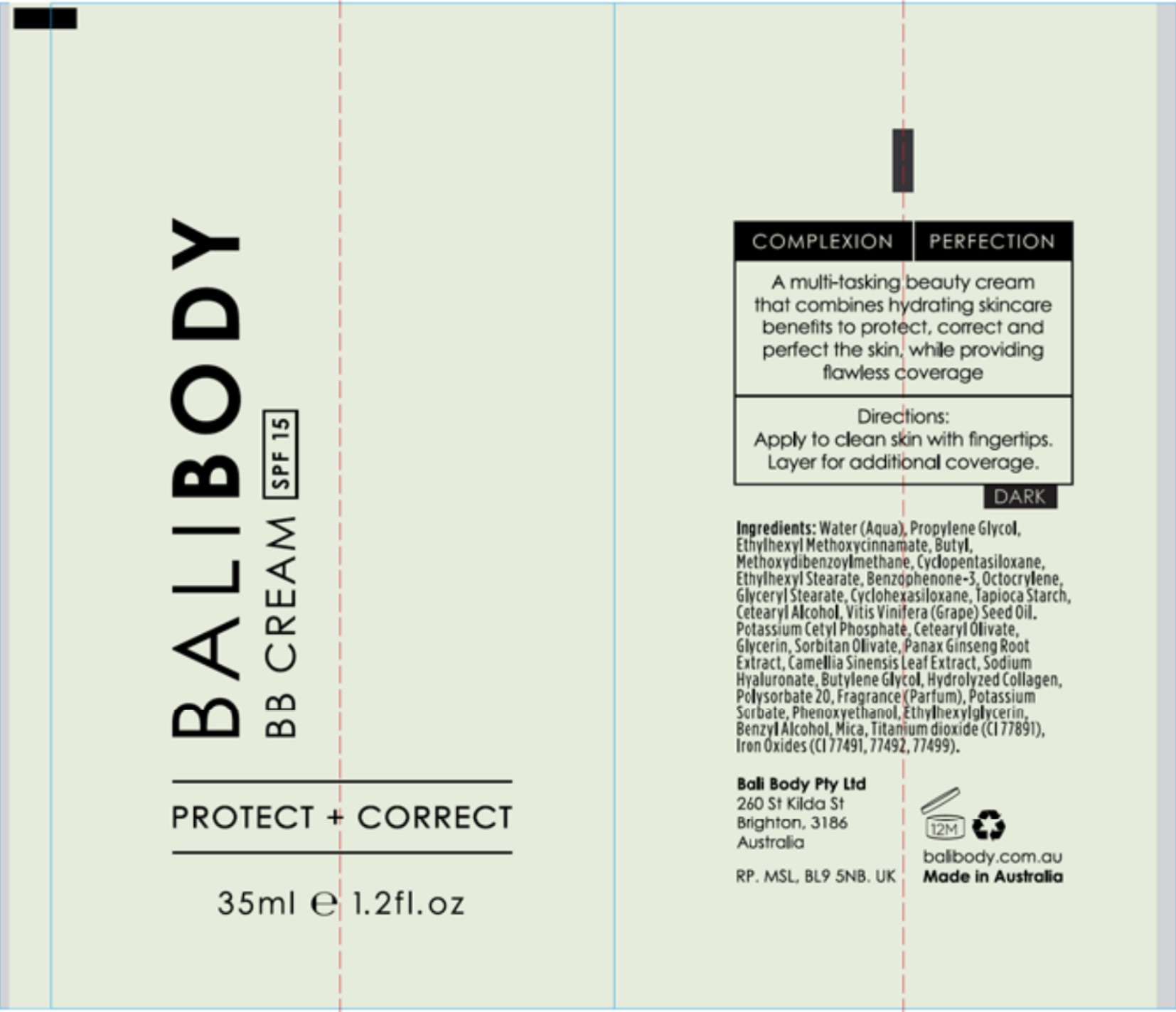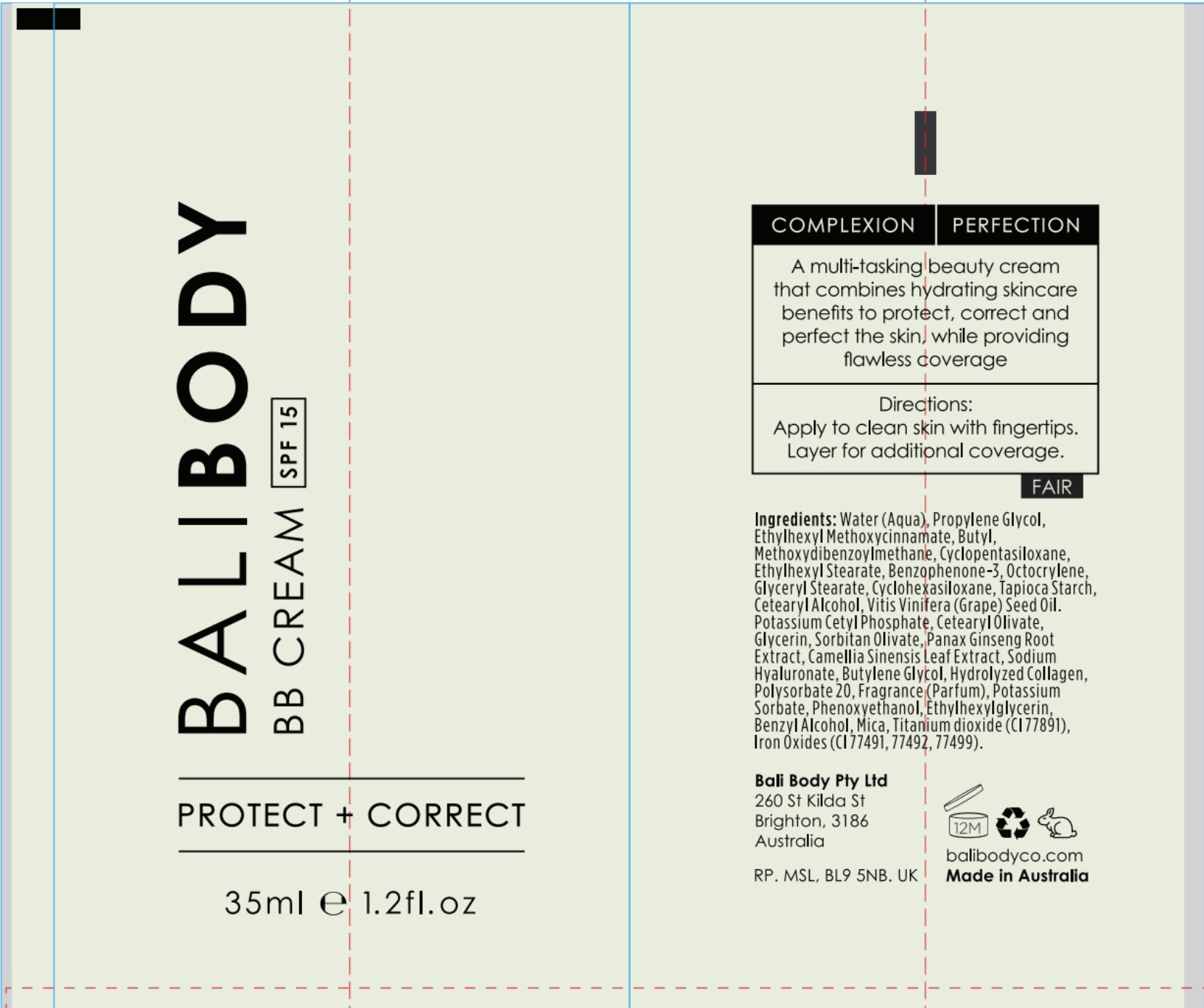 DRUG LABEL: Bali Body BB Cream SPF 15
NDC: 70630-1605 | Form: CREAM
Manufacturer: Bali Body Pty Ltd
Category: otc | Type: HUMAN OTC DRUG LABEL
Date: 20210106

ACTIVE INGREDIENTS: OCTOCRYLENE 2.7 mg/100 mL; AVOBENZONE 4 mg/100 mL; OCTINOXATE 4 mg/100 mL; OXYBENZONE 3 mg/100 mL
INACTIVE INGREDIENTS: GRAPE SEED OIL; CYCLOMETHICONE 5; WATER; STARCH, TAPIOCA; ASIAN GINSENG; BUTYLENE GLYCOL; POTASSIUM SORBATE; ETHYLHEXYLGLYCERIN; MICA; TITANIUM DIOXIDE; CETOSTEARYL ALCOHOL; CETEARYL OLIVATE; GREEN TEA LEAF; HYALURONATE SODIUM; PHENOXYETHANOL; POTASSIUM CETYL PHOSPHATE; POLYSORBATE 20; BENZYL ALCOHOL; GLYCERIN; SORBITAN OLIVATE; PROPYLENE GLYCOL; ETHYLHEXYL STEARATE; FERROUS OXIDE; CYCLOMETHICONE 6; GLYCERYL MONOSTEARATE

Bali Body BB Cream SPF 15 (Available in 4 Shades)

PACKAGE LABEL

ACTIVE INGREDIENT

Octinoxate 4%

Avobenzone 4%

Oxybenzone 3%

Octocrylene 2.7%

Keep out of reach of children.

PURPOSE

A multi-tasking beauty cream.

Provides SPF 15 protection.

INDICATIONS AND USAGE

Shake well before use. Apply liberaly 15 minutes before sun exposure.

Children under 6 months old: Ask a doctor.

Re-apply every 2 hours.

Use water-resistant sunscreen if swimming or sweating.

Store in cool dry place.

WARNINGS

Skin Cancer/Skin Ageing Alert: Spending time in the sun increases your risk of skin cancer and early skin aging.

This product has been shown only to help prevent sunburn, not skin cancer or early skin aging.

Do not use on damaged or broken skin.

When using this product keep out of eyes. Rinse with water to remove.

Stop use and ask a doctor if rash occurs.

Always wear a hat, protective clothing and sunglasses.

DOSAGE AND ADMINISTRATION

Apply liberally 15 minutes before sun exposure.